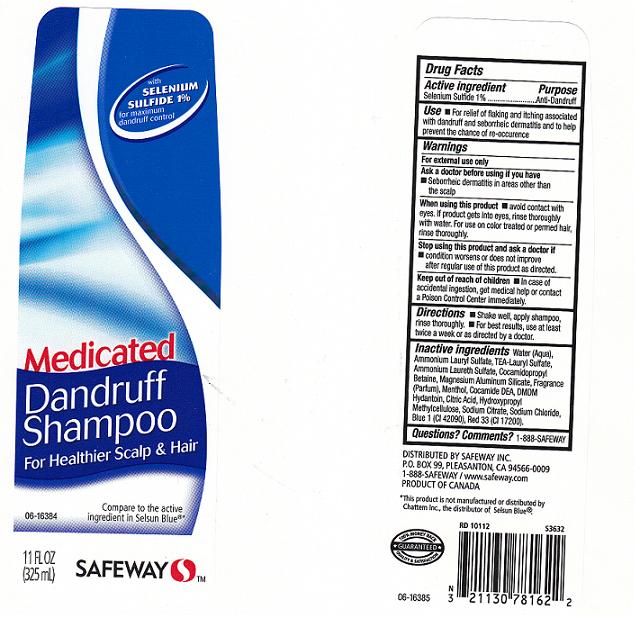 DRUG LABEL: ANTIDANDRUFF 
NDC: 21130-610 | Form: SHAMPOO
Manufacturer: SAFEWAY INC
Category: otc | Type: HUMAN OTC DRUG LABEL
Date: 20100805

ACTIVE INGREDIENTS: SELENIUM SULFIDE 1.0000 mL/100 mL

Drug Facts Box - Back Label

ACTIVE INGREDIENT

SELENIUM SULFIDE 1% (ANTI DANDRUFF)

USES AND DIRECTIONS

- USES: FOR RELIEF OF FLAKING AND ITCHING DUE TO DANDRUFF, AND SEBORRHEIC DERMATITIS, AND TO HELP PREVENT THE CHANCE OF RE-OCCURRENCE.

- DIRECTIONS:SHAKE WELL, SHAMPOO, THEN RINSE THOROUGHLY. FOR BEST RESULTS, USE AT LEAST TWICE A WEEK OR AS DIRECTED BY A DOCTOR.

WARNINGS

- FOR EXTERNAL USE ONLY.

ASK A DOCTOR BEFORE USING IF YOU HAVE

SEBORRHEIC DERMATITIS IN AREAS OTHER THAN THE SCALP

WHEN USING THIS PRODUCT

- AVOID CONTACT WITH THE EYES. IF CONTACT OCCURS, RINSE EYES THOROUGHLY WITH WATER. FOR USE ON COLOR-TREATED OR PERMED HAIR, RINSE THOROUGHLY.

STOP USE AND ASK A DOCTOR IF

- CONDITION WORSENS OR DOES NOT IMPROVE AFTER REGULAR USE OF THIS PRODUCT AS DIRECTED.

KEEP OUT OF REACH OF CHILDREN

- IF SWALLOWED, GET MEDICAL HELP OR CONTACT A POISON CONTROL CENTER RIGHT AWAY.

PACKAGE FRONT AND BACK LABELS

11OZ FRONT AND BACK LABELS: safeway11.jpg

QUESTIONS/COMMENTS?

1 - 888 - SAFEWAY